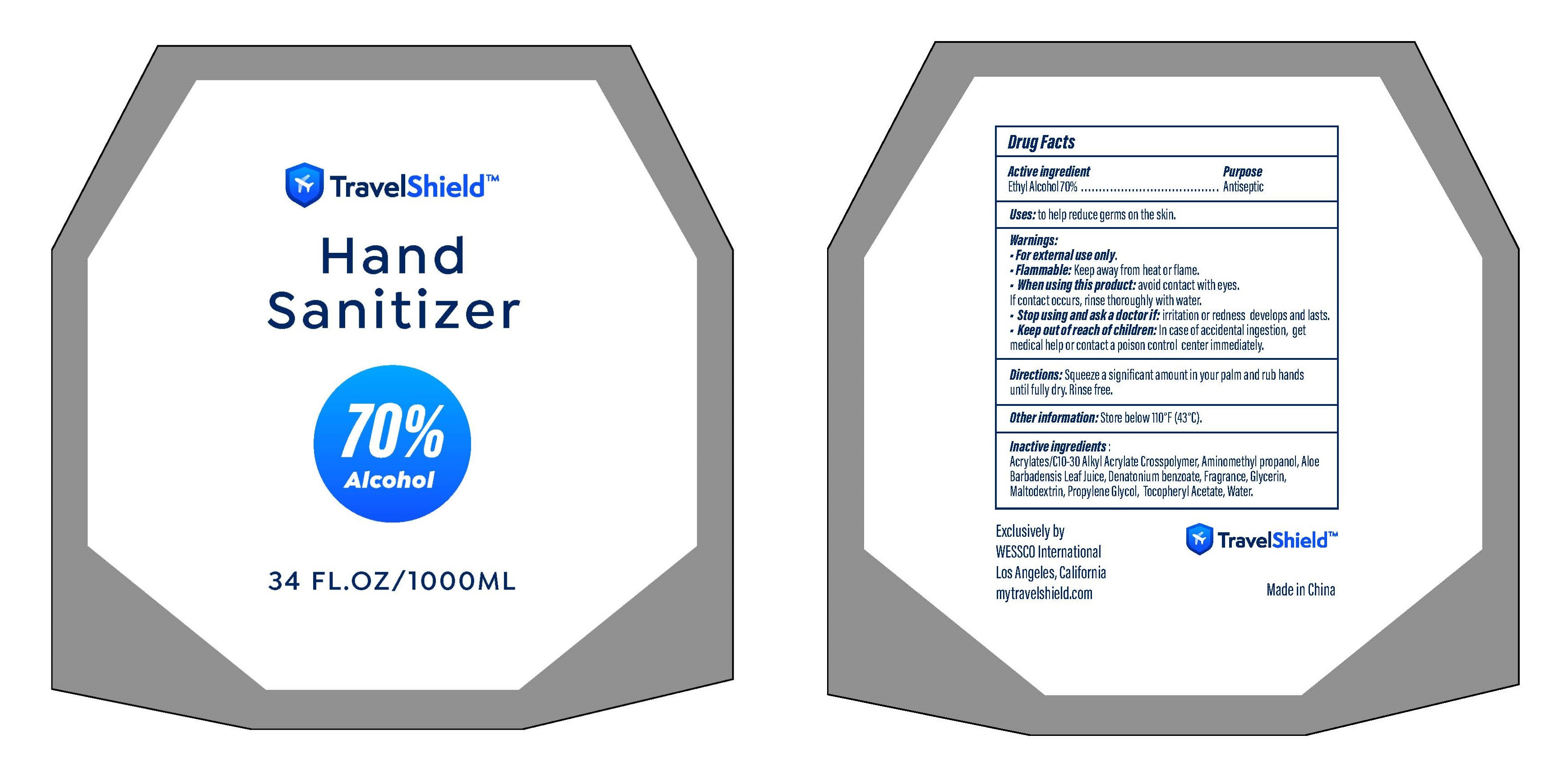 DRUG LABEL: Hand Sanitizer
NDC: 42509-034 | Form: GEL
Manufacturer: Wessco International
Category: otc | Type: HUMAN OTC DRUG LABEL
Date: 20200704

ACTIVE INGREDIENTS: ALCOHOL 70 mL/100 mL
INACTIVE INGREDIENTS: PROPYLENE GLYCOL; MALTODEXTRIN; WATER; ALOE VERA LEAF; GLYCERIN; CARBOMER INTERPOLYMER TYPE A (55000 CPS); AMINOMETHYLPROPANOL; .ALPHA.-TOCOPHEROL ACETATE; DENATONIUM BENZOATE

Active ingredient
Ethyl Alcohol 70%

Purpose
Antiseptic

INDICATIONS AND USAGE

Uses: to help reduce germs on the skin

WARNINGS

Warnings: For external use only, Flammable, Keep away from fire or flame

When using this product: avoid contact with eyes, if contact occurs, rinse thoroughly with water.

STOP USE

Stop using and ask a doctor: if irritation or redness develops and lasts.

Keep out of reach of children: In case of accidental ingetion, get medical help or contact a poison control center immediately.

DOSAGE AND ADMINISTRATION

Directions: Squeeze a significant amount in your palm and rub hands until fully dry. Rinse free.

Other information: Store below 110︒F(43︒C)

Inactive ingredients

Acrylate/C10-30 Alkyl Acrylate crosspolymer, Aloe Barbadensis Leaf Juice, Aminomethyl propanol，Denatonium benzoate, Fragrance, Glycerin, Maltodextrin, Propylene Glycol, Tocopheryl Acetate, Water.